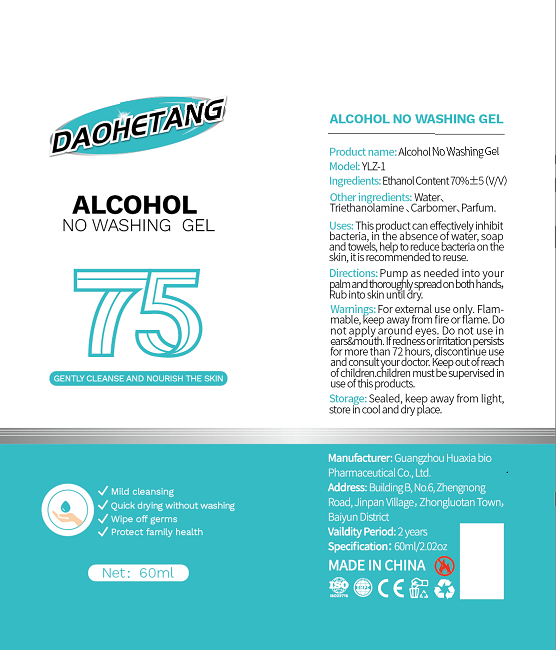 DRUG LABEL: Alcohol NO WASHING Gel
NDC: 40402-001 | Form: GEL
Manufacturer: Guangzhou Huaxia Biopharmaceutical Co., Ltd.
Category: otc | Type: HUMAN OTC DRUG LABEL
Date: 20200429

ACTIVE INGREDIENTS: ALCOHOL 42 mL/60 mL
INACTIVE INGREDIENTS: CARBOXYPOLYMETHYLENE; WATER; TROLAMINE

DOSAGE AND ADMINISTRATION

Sealed, keep away from light,store incool and dry place.

INACTIVE INGREDIENT

Water、 Triethanolamine 、Carbomer、Parfum

INDICATIONS AND USAGE

Pump as needed into your palmandthoroughlyspreadonbothhands,Rubinto skin untl dry.

ACTIVE INGREDIENT

ALCOHOL

keep out of reach of children

PURPOSE

Disinfection
Sterilization
No Rinseing

WARNINGS

For extemal use only. Flam-mable, keep away from fire or flame. Do not apply around eyes. DO not use in ears&mouth. If rednessorinitationpersists for more than 72 hours, disoontinue use and consultyour doctor. Keepoutofreach of children.children mustbesupervised in use of this products.